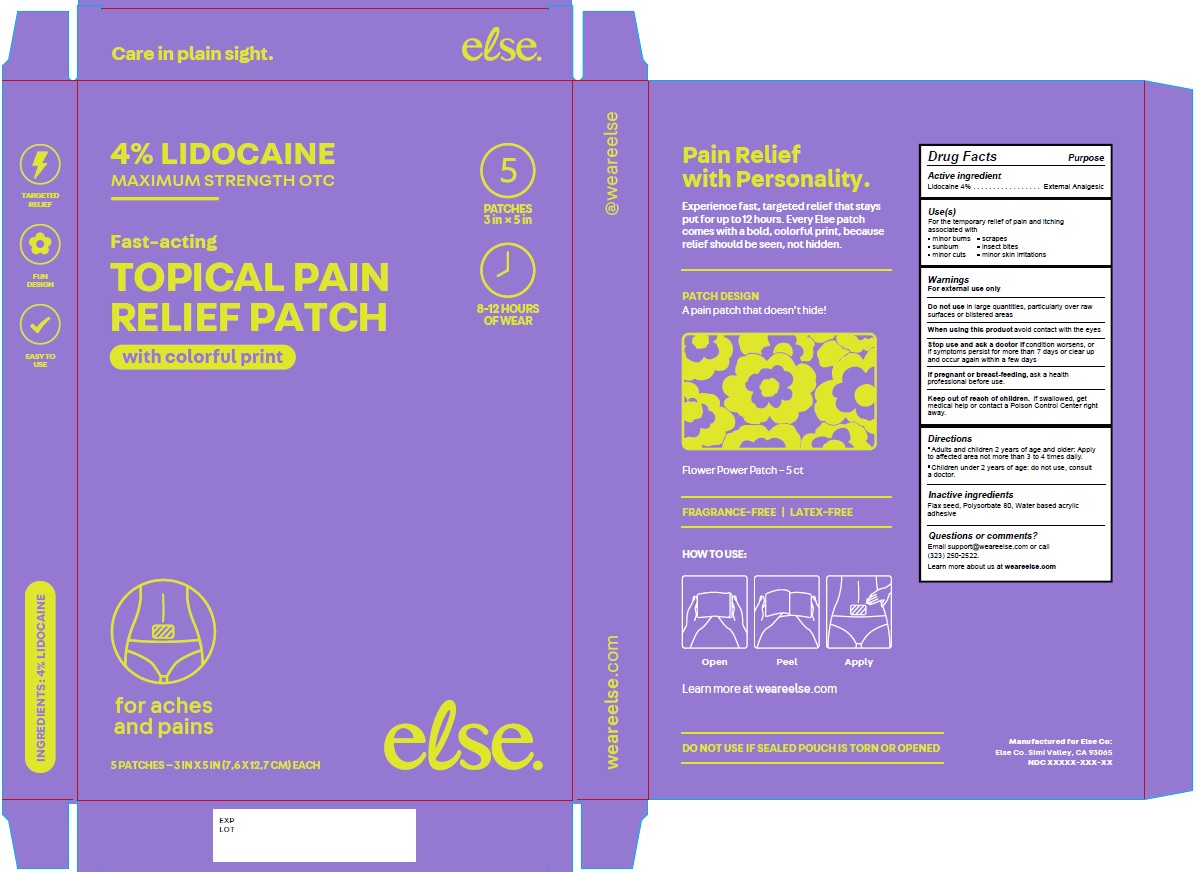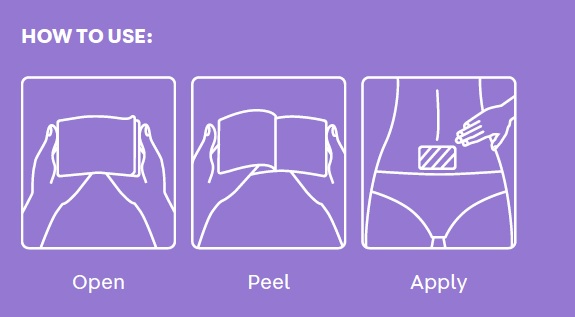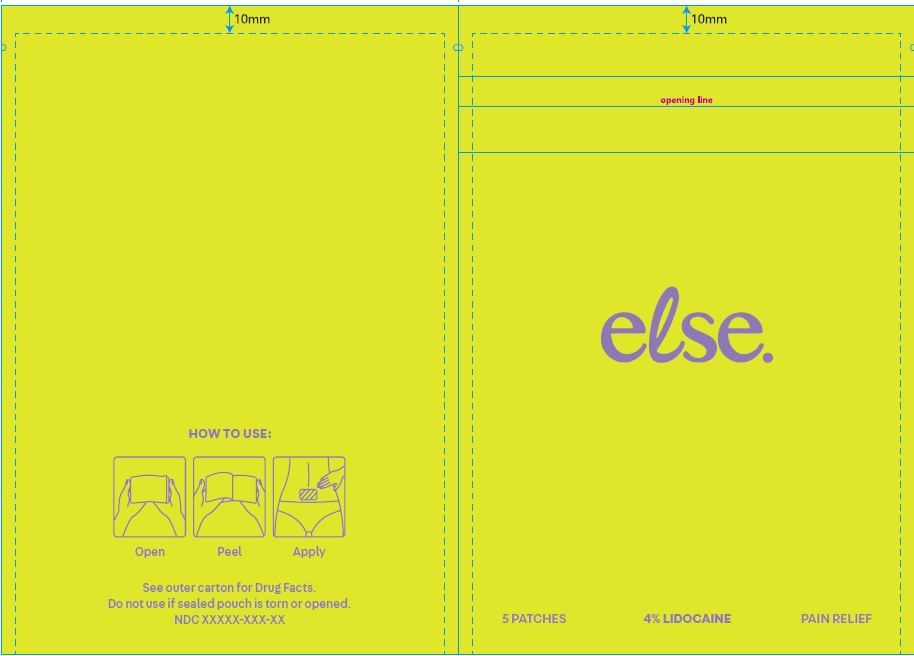 DRUG LABEL: else.
NDC: 85981-001 | Form: PATCH
Manufacturer: Else Co.
Category: otc | Type: HUMAN OTC DRUG LABEL
Date: 20250828

ACTIVE INGREDIENTS: LIDOCAINE 4 g/100 g
INACTIVE INGREDIENTS: FLAX SEED; POLYSORBATE 80

Topical Pain Relief Patch

Active ingredient

Lidocaine 4%

Purpose

External Analgesic

Uses

For the temporary relief of pain and itching associated with

- minor burns • scrapes
- sunburn • insect bites
- minor cuts • minor skin irritations

Warnings

For external use only

Do not use in large quantities, particularly over raw surfaces or blistered areas

When using this product avoid contact with the eyes

Stop use and ask a doctor if condition worsens, or if symptoms persist for more than 7 days or clear up and occur again within a few days

PREGNANCY OR BREAST FEEDING

If pregnant or breast-feeding, ask a health professional before use.

Keep out of reach of children. If swallowed, get medical help or contact a Poison Control Center right away.

Directions

- Adults and children 2 years of age and older: Apply to affected area not more than 3 to 4 times daily.
- Children under 2 years of age: do not use, consult a doctor.

Inactive ingredients
Flax seed, Polysorbate 80, Water based acrylic adhesive

Questions or comments?

Email support@weareelse.com or call
(323) 250-2522.
Learn more about us at weareelse.com

FRAGRANCE-FREE

LATEX-FREE

Manufactured for Else Co:

Else Co. Simi Valley, CA 93065

PACKAGE LABEL

4% LIDOCAINE

MAXIMUM STRENGTH OTC

Fast-acting

TOPICAL PAIN

RELIEF PATCH

with colorful print

8-12 HOURS OF WEAR

for aches and pains

5 PATCHES - 3 IN X 5 IN (7.6 X 12.7 CM) EACH

else.